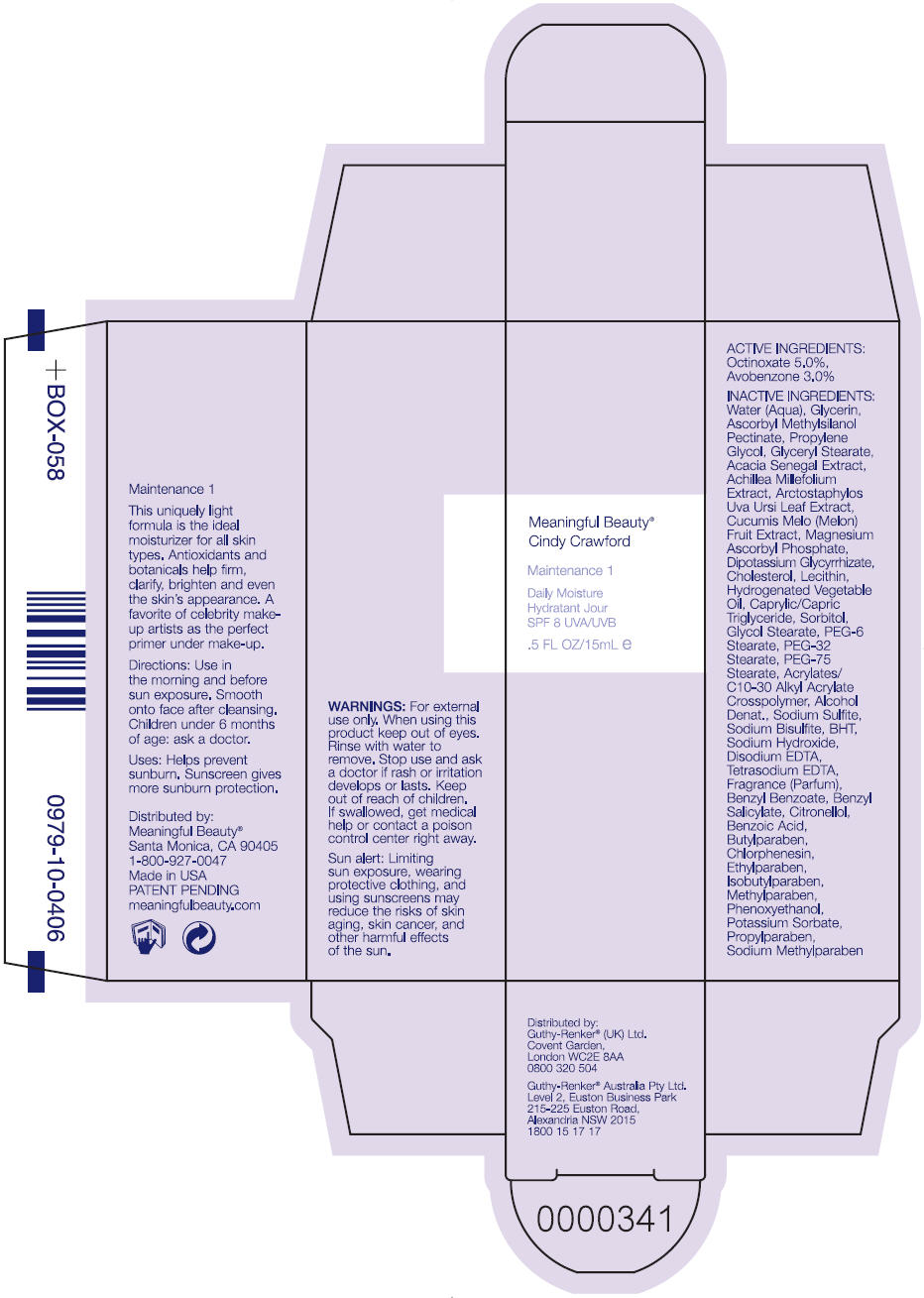 DRUG LABEL: Meaningful Beauty Cindy Crawford Maintenance 1 Daily Moisture SPF 8
NDC: 70605-019 | Form: LOTION
Manufacturer: Guthy-Renker LLC
Category: otc | Type: HUMAN OTC DRUG LABEL
Date: 20160901

ACTIVE INGREDIENTS: OCTINOXATE 5 mg/100 mL; AVOBENZONE 3 mg/100 mL
INACTIVE INGREDIENTS: WATER; GLYCERIN; PROPYLENE GLYCOL; GLYCERYL MONOSTEARATE; GLYCYRRHIZINATE DIPOTASSIUM; CHOLESTEROL; LECITHIN, SOYBEAN; MEDIUM-CHAIN TRIGLYCERIDES; SORBITOL; GLYCOL STEARATE; ALCOHOL; SODIUM SULFITE; SODIUM BISULFITE; BUTYLATED HYDROXYTOLUENE; SODIUM HYDROXIDE; EDETATE DISODIUM; EDETATE SODIUM; BENZYL BENZOATE; BENZYL SALICYLATE; .BETA.-CITRONELLOL, (R)-; BENZOIC ACID; BUTYLPARABEN; CHLORPHENESIN; ETHYLPARABEN; ISOBUTYLPARABEN; METHYLPARABEN; PHENOXYETHANOL; POTASSIUM SORBATE; PROPYLPARABEN

Meaningful Beauty® Cindy Crawford Maintenance 1 Daily Moisture SPF 8

Drug Facts

Active Ingredient

Octinoxate | 5.0%
Avobenzone | 3.0%

Uses

PURPOSE

helps prevent sunburn. Sunscreen gives more sunburn protection.

Warnings

For external use only. When using this product keep out of eyes. Rinse with water to remove. Stop use and ask a doctor if rash or irritation develops or lasts.

Keep out of reach of children. If swallowed, get medical help or contact a Poison Control Center right away.

Sun alert

Limiting sun exposure, wearing protective clothing, and using sunscreens may reduce the risks of skin aging, skin cancer, and other harmful effects of the sun.

Directions

Use in the morning and before sun exposure. Smooth onto face after cleansing. Children under 6 months of age: ask a doctor.

Inactive Ingredients

Water (Aqua), Glycerin, Ascorbyl Methylsilanol Pectinate, Propylene Glycol, Glyceryl Stearate, Acacia Senegal Extract, Achillea Millefolium Extract, Arctostaphylos Uva Ursi Leaf Extract, Cucumis Melo (Melon) Fruit Extract, Magnesium Ascorbyl Phosphate, Dipotassium Glycyrrhizate, Cholesterol, Lecithin, Hydrogenated Vegetable Oil, Caprylic/Capric Triglyceride, Sorbitol, Glycol Stearate, PEG-6 Stearate, PEG-32 Stearate, PEG-75 Stearate, Acrylates/C10-30 Alkyl Acrylate Crosspolymer, Alcohol Denat., Sodium Sulfite, Sodium Bisulfite, BHT, Sodium Hydroxide, Disodium EDTA, Tetrasodium EDTA, Fragrance (Parfum), Benzyl Benzoate, Benzyl Salicylate, Citronellol, Benzoic Acid, Butylparaben, Chlorphenesin, Ethylparaben, Isobutylparaben, Methylparaben, Phenoxyethanol, Potassium Sorbate, Propylparaben, Sodium Methylparaben

Distributed by:
Guthy-Renker® (UK) Ltd.
Covent Garden,
London WC2E 8AA
0800 320 504

PRINCIPAL DISPLAY PANEL - 15 mL Bottle Box

Meaningful Beauty®
Cindy Crawford

Maintenance 1

Daily Moisture
SPF 8 UVA/UVB

.5 FL OZ/15mL e